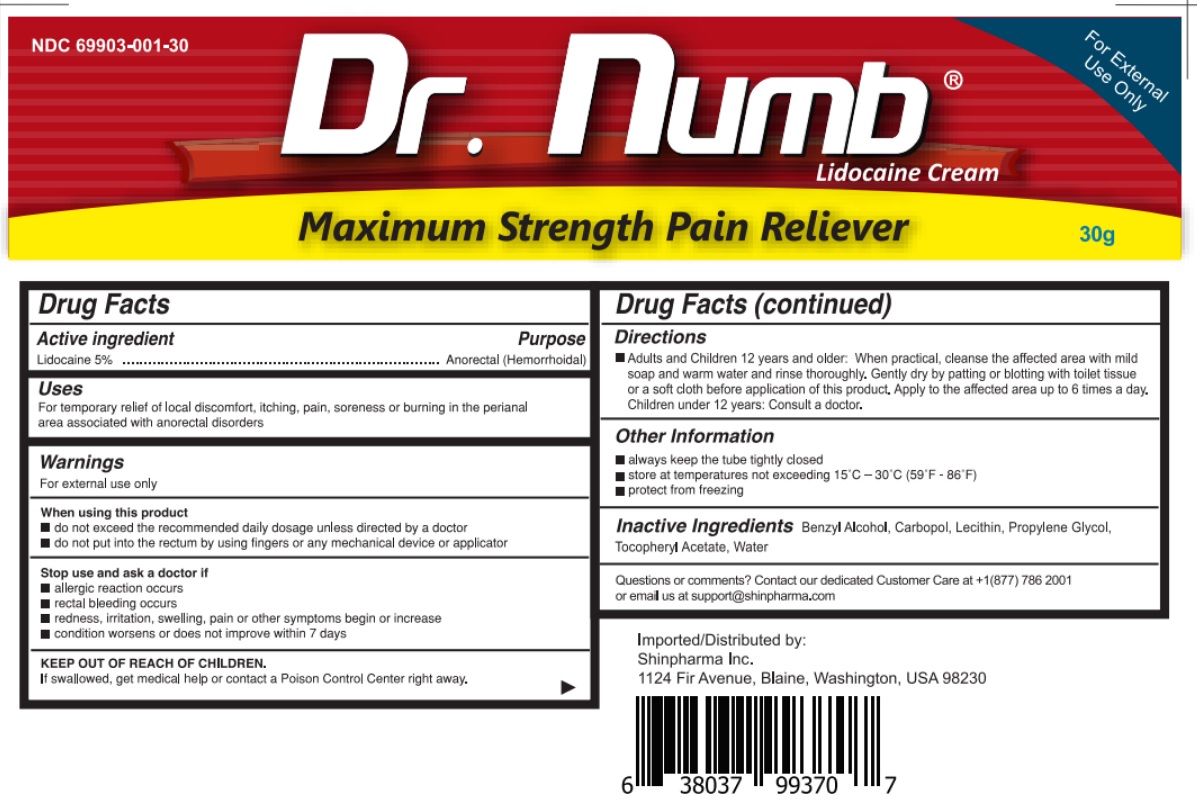 DRUG LABEL: Dr. Numb
NDC: 69903-001 | Form: CREAM
Manufacturer: Shinpharma Inc
Category: otc | Type: HUMAN OTC DRUG LABEL
Date: 20240403

ACTIVE INGREDIENTS: LIDOCAINE 1.5 g/30 g
INACTIVE INGREDIENTS: BENZYL ALCOHOL; CARBOMER HOMOPOLYMER, UNSPECIFIED TYPE; LECITHIN, SOYBEAN; PROPYLENE GLYCOL BUTYL ETHER; TOCOPHERYL RETINOATE; WATER

Drug Facts

Active ingredient

Lidocaine 5%

Purpose

Anorectal (Hemmorhoidal)

Uses

For temporary relief of local discomfort, itching, pain, soreness or burning in the perianal area associated with anorectal disorders.

Warnings

For external use only

When using this product

- do not exceed the recommended daily dosage unless directed by a doctor
- do not put into the rectum by using fingers or any mechanical device or applicator

Stop the use and consult doctor if

- allergic reaction occurs
- rectal bleeding occurs
- redness, irritation, swelling, pain, or other symptoms begin or increase
- condition worsens or does not improve within 7 days

keep out of reach of children

If swallowed, get medical help or contact a Poison Control Center right away

Directions

- Adults and Children 12 years and older: When practical, cleanse the affected area with mild soap and warm water and rinse thoroughly. Gently dry by patting or blotting with tissue or a soft cloth before application of product. Apply to the affected area upto 6 times a day
- Children under 12 years of age: Consult a doctor

Other information

- always keep the tube tightly closed
- store at temperature not exceeding 15°C - 30°C (59°F - 86°F)
- protect from freezing

Inactive Ingredients

Benzyl Alcohol, Carbopol, Lecithin, Propylene Glycol, Tocopheryl Acetate, Water.

Question or comments

Contact our dedicated Customer Care at 1-877-786-2001 or email us at support@shinpharma.com

Principal Display Panel

NDC 69903-001-30

Prompt, Soothing Relief from Painful Burning, Itching and Discomfort

5% Lidocaine Cream

For External Use Only

Dr. Numb Lidocaine Cream

RAPID ABSORPTION

Maximum Strength Pain Reliever

30g